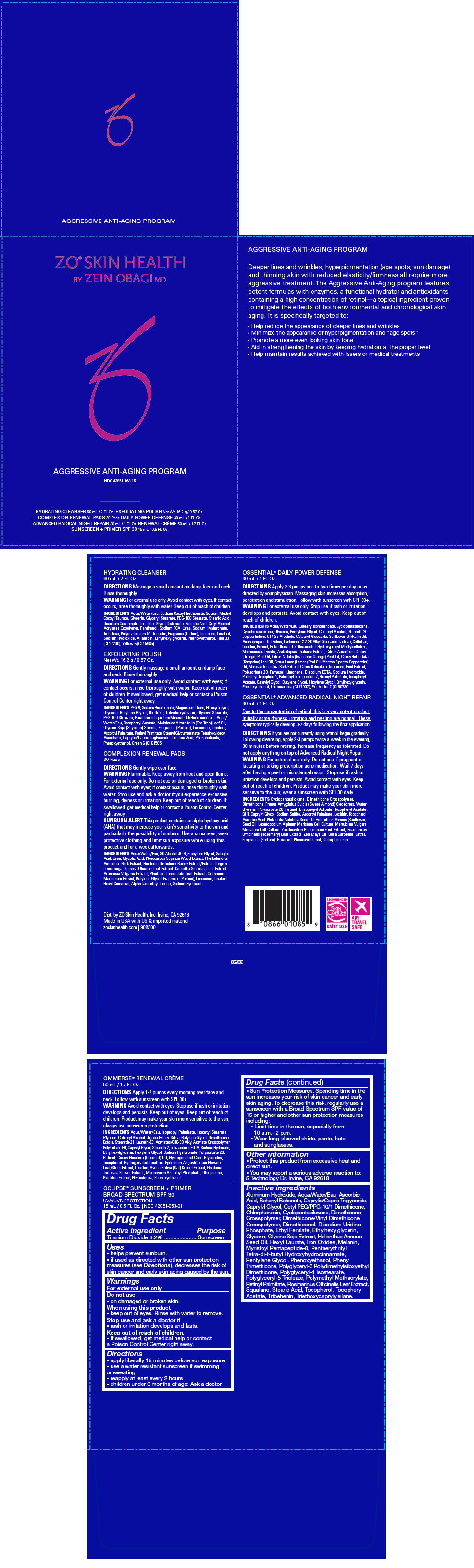 DRUG LABEL: ZO SKIN HEALTH Aggressive Anti-Aging Program		
NDC: 42851-168 | Form: KIT | Route: TOPICAL
Manufacturer: ZO Skin Health, Inc.
Category: otc | Type: HUMAN OTC DRUG LABEL
Date: 20200618

ACTIVE INGREDIENTS: TITANIUM DIOXIDE 82 mg/1 mL
INACTIVE INGREDIENTS: ALUMINUM HYDROXIDE; WATER; ASCORBIC ACID; BEHENYL BEHENATE; MEDIUM-CHAIN TRIGLYCERIDES; CAPRYLYL GLYCOL; CETYL PEG/PPG-10/1 DIMETHICONE (HLB 2); CHLORPHENESIN; CYCLOMETHICONE 5; DIMETHICONE CROSSPOLYMER (450000 MPA.S AT 12% IN CYCLOPENTASILOXANE); DIMETHICONE/VINYL DIMETHICONE CROSSPOLYMER (SOFT PARTICLE); DIMETHICONOL (100000 CST); URIDINE MONOPHOSPHATE DISODIUM; ETHYL FERULATE; ETHYLHEXYLGLYCERIN; GLYCERIN; SUNFLOWER OIL; HEXYL LAURATE; FERRIC OXIDE RED; MELANIN SYNTHETIC (TYROSINE, PEROXIDE); PENTAERYTHRITOL TETRAKIS(3-(3,5-DI-TERT-BUTYL-4-HYDROXYPHENYL)PROPIONATE); PENTYLENE GLYCOL; PHENOXYETHANOL; PHENYL TRIMETHICONE; POLYGLYCERYL-3 POLYDIMETHYLSILOXYETHYL DIMETHICONE (4000 MPA.S); POLYGLYCERYL-4 ISOSTEARATE; POLY(METHYL METHACRYLATE; 450000 MW); VITAMIN A PALMITATE; ROSEMARY; SQUALANE; STEARIC ACID; TOCOPHEROL; .ALPHA.-TOCOPHEROL ACETATE; TRIBEHENIN; TRIETHOXYCAPRYLYLSILANE

ZO® SKIN HEALTH Aggressive Anti-Aging Program
NDC 42851-168

Drug Facts

Active ingredient

Titanium Dioxide 8.2%

Purpose

Sunscreen

Uses

- helps prevent sunburn.
- if used as directed with other sun protection measures (see Directions), decreases the risk of skin cancer and early skin aging caused by the sun.

Warnings

For external use only.

Do not use

- on damaged or broken skin.

When using this product

- keep out of eyes. Rinse with water to remove.

Stop use and ask a doctor if

- rash or irritation develops and lasts.

Keep out of reach of children.

- If swallowed, get medical help or contact a Poison Control Center right away.

Directions

- apply liberally 15 minutes before sun exposure
- use a water resistant sunscreen if swimming or sweating
- reapply at least every 2 hours
- children under 6 months of age: Ask a doctor
- Sun Protection Measures. Spending time in the sun increases your risk of skin cancer and early skin aging. To decrease this risk, regularly use a sunscreen with a Broad Spectrum SPF value of 15 or higher and other sun protection measures including:
  - Limit time in the sun, especially from 10 a.m.- 2 p.m.
  - Wear long-sleeved shirts, pants, hats and sunglasses.

Other information

- Protect this product from excessive heat and direct sun.
- You may report a serious adverse reaction to: 5 Technology Dr. Irvine, CA 92618

Inactive ingredients

Aluminum Hydroxide, Aqua/Water/Eau, Ascorbic Acid, Behenyl Behenate, Caprylic/Capric Triglyceride, Caprylyl Glycol, Cetyl PEG/PPG-10/1 Dimethicone, Chlorphenesin, Cyclopentasiloxane, Dimethicone Crosspolymer, Dimethicone/Vinyl Dimethicone Crosspolymer, Dimethiconol, Disodium Uridine Phosphate, Ethyl Ferulate, Ethylhexylglycerin, Glycerin, Glycine Soja Extract, Helianthus Annuus Seed Oil, Hexyl Laurate, Iron Oxides, Melanin, Myristoyl Pentapeptide-8, Pentaerythrityl Tetra-di-t-butyl Hydroxyhydrocinnamate, Pentylene Glycol, Phenoxyethanol, Phenyl Trimethicone, Polyglyceryl-3 Polydimethylsiloxyethyl Dimethicone, Polyglyceryl-4 Isostearate, Polyglyceryl-5 Trioleate, Polymethyl Methacrylate, Retinyl Palmitate, Rosmarinus Officinalis Leaf Extract, Squalane, Stearic Acid, Tocopherol, Tocopheryl Acetate, Tribehenin, Triethoxycaprylylsilane.

Dist. by ZO Skin Health, Inc. Irvine, CA 92618

PRINCIPAL DISPLAY PANEL - Kit Carton

ZO® SKIN HEALTH
BY ZEIN OBAGI MD

AGGRESSIVE ANTI-AGING PROGRAM
NDC 42851-168-15

HYDRATING CLEANSER 60 mL / 2 Fl. Oz. EXFOLIATING POLISH Net Wt. 16.2 g / 0.57 Oz.
COMPLEXION RENEWAL PADS 30 Pads DAILY POWER DEFENSE 30 mL / 1 Fl. Oz.
ADVANCED RADICAL NIGHT REPAIR 30 mL / 1 Fl. Oz. RENEWAL CRÈME 50 mL / 1.7 Fl. Oz.
SUNSCREEN + PRIMER SPF 30 15 mL / 0.5 Fl. Oz.